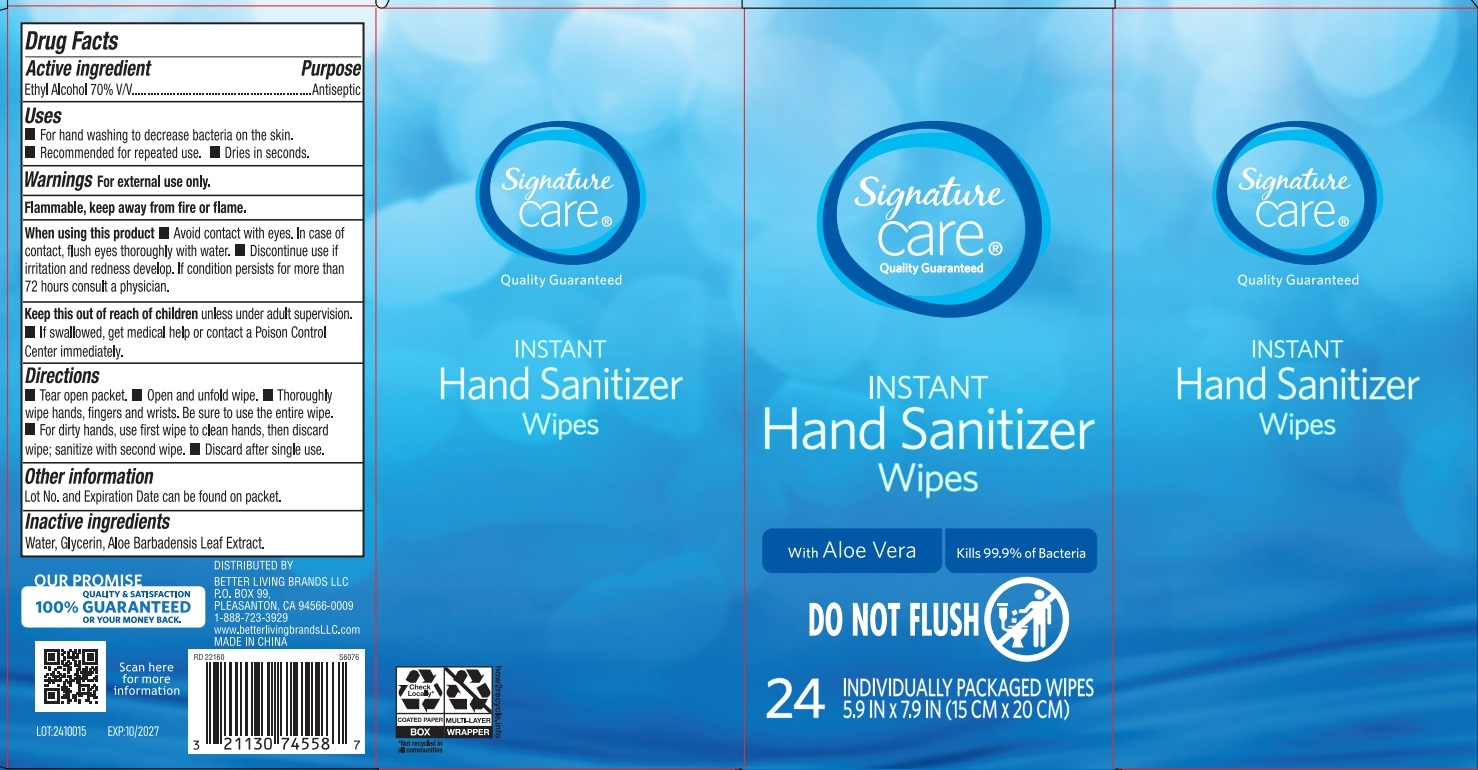 DRUG LABEL: Signature Care Hand Sanitizer Wipes with Aloe Vera
NDC: 21130-145 | Form: CLOTH
Manufacturer: Better Living Brands LLC
Category: otc | Type: HUMAN OTC DRUG LABEL
Date: 20241119

ACTIVE INGREDIENTS: ALCOHOL 70 g/100 g
INACTIVE INGREDIENTS: WATER; ALOE VERA LEAF; GLYCERIN

HAND SANITIZER WIPES

Active ingredient

Ethyl Alcohol 70% v/v

Purpose

Antiseptic

Use

- For hand washing to decrease bacteria on the skin.
- Recommended for repeaed use.
- Dries in seconds.

Warnings

For external use only

Flammable.Keep away from fire and flame.

When using this product

- Avoid contact with eyes. In case of contact with eyes, fllush thoroughly with water.
- Discontinue use if irritation and redness develop. If condition persists for more than 72 hours consult a physician.

Other Information

- Lot No. and Expiration date can be found on packet.

Keep out of reach of children.

unless under adult supervision.

- If swallowed, get medical help or contact a Poison Control Center right away.

Directions

- Tear open packet.
- Open and unfold wipe.
- Thoroughly wipe hands, fingers and wrists. Be sure to use the entire wipe.
- For dirty hads, use first wipe to clean hands, then discard wipe; sanitize with second wipe.
- Discard after single use.

Inactive ingredients

Water, Glycerin, Aloe Barbadensis Leaf Extract

1-888-723-3929